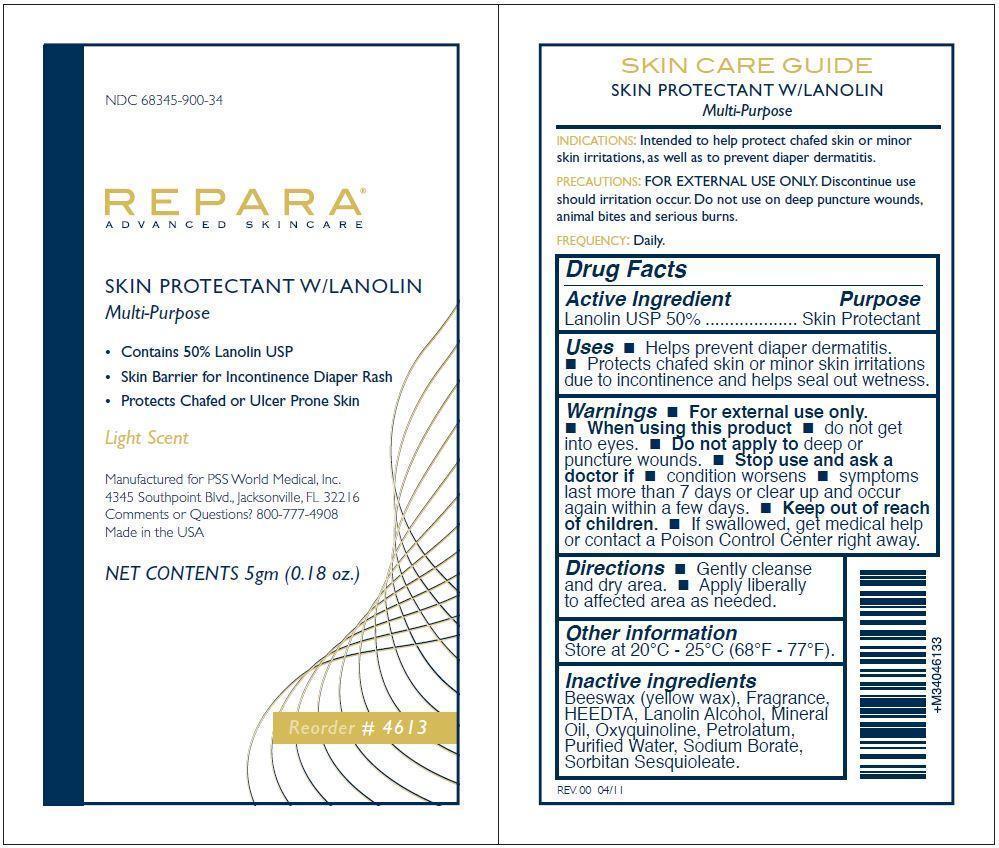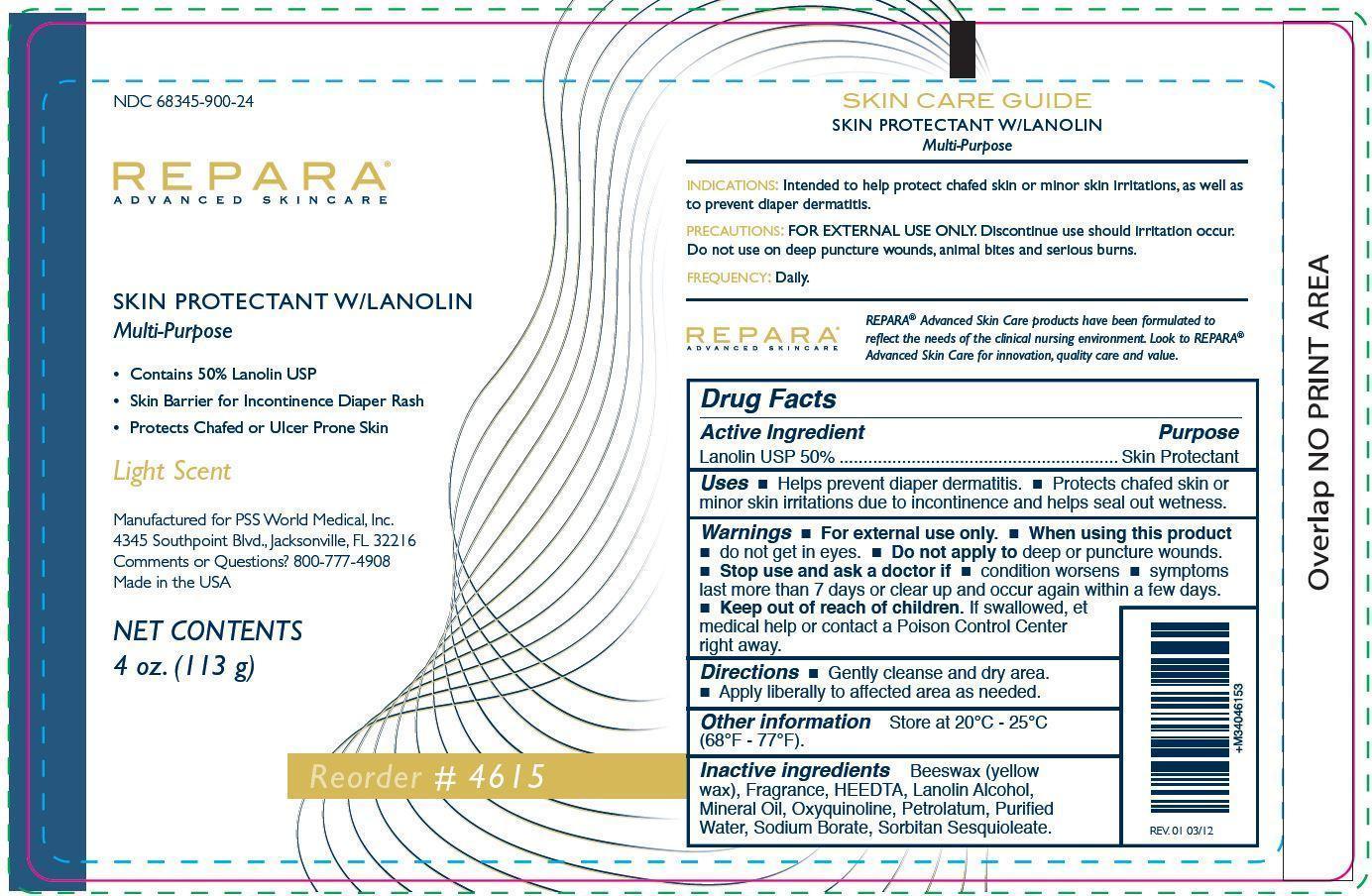 DRUG LABEL: Repara
NDC: 68345-818 | Form: OINTMENT
Manufacturer: PSS World Medical, Inc.
Category: otc | Type: HUMAN OTC DRUG LABEL
Date: 20140807

ACTIVE INGREDIENTS: LANOLIN 5 g/10 g
INACTIVE INGREDIENTS: YELLOW WAX; HYDROXYETHYLETHYLENEDIAMINETRIACETIC ACID; LANOLIN ALCOHOLS; MINERAL OIL; OXYQUINOLINE; PETROLATUM; WATER; SODIUM BORATE; SORBITAN SESQUIOLEATE

Active Ingredient Purpose

Lanolin USP 50% .................. Skin Protectant

PURPOSE

Repara Advanced Skincare

Skin Protectant w/ Lanolin

Multi-Purpose

- Contains 50% Lanolin USP
- Skin Barrier for Incontinence Diaper Rash
- Protects chafed or ulcer prone skin

Light Scent

Keep out of reach of children. If swallowed, get medical help or contact a Poison Control Center right away.

Directions

- Gently cleanse and dry area.
- Apply liberally to affected area as needed.

Warnings

- For external use only
- When using this product
- do not get into eyes.
- Do not apply to deep or puncture wounds.
- Stop use and ask a doctor if
- condition worsens
- symptoms last more than 7 days or clear up and occur again within a few days.

INDICATIONS AND USAGE

Indications: Intended to help protect chafed skin or minor skin irritations, as well as to prevent diaper dermatitis.

Precautions: FOR EXTERNAL USE ONLY. Discontinue use should irritation occur. Do not use on deep puncture wounds, animal bites, and serious burns.

Frequency: Daily.

Uses

- Helps prevent diaper dermatitis.
- Protects chafed skin or minor skin irritations due to incontinence and helps seal out wetness.

Inactive Ingredients

beeswax (yellow wax), fragrance, HEEDTA, lanolin alcohol, mineral oil, oxyquinolone, petrolatum, purified water, sodium borate, sorbitan sesquioleate.

OTHER SAFETY INFORMATION

Manufactured for PSS World Medical, Inc.

4345 Southpoint Blvd., Jacksonville, FL 32216

Comments or Questions? 800-777-4908

Made in the USA

Other Information

Store at 20oC - 25oC (68oF - 77oF).